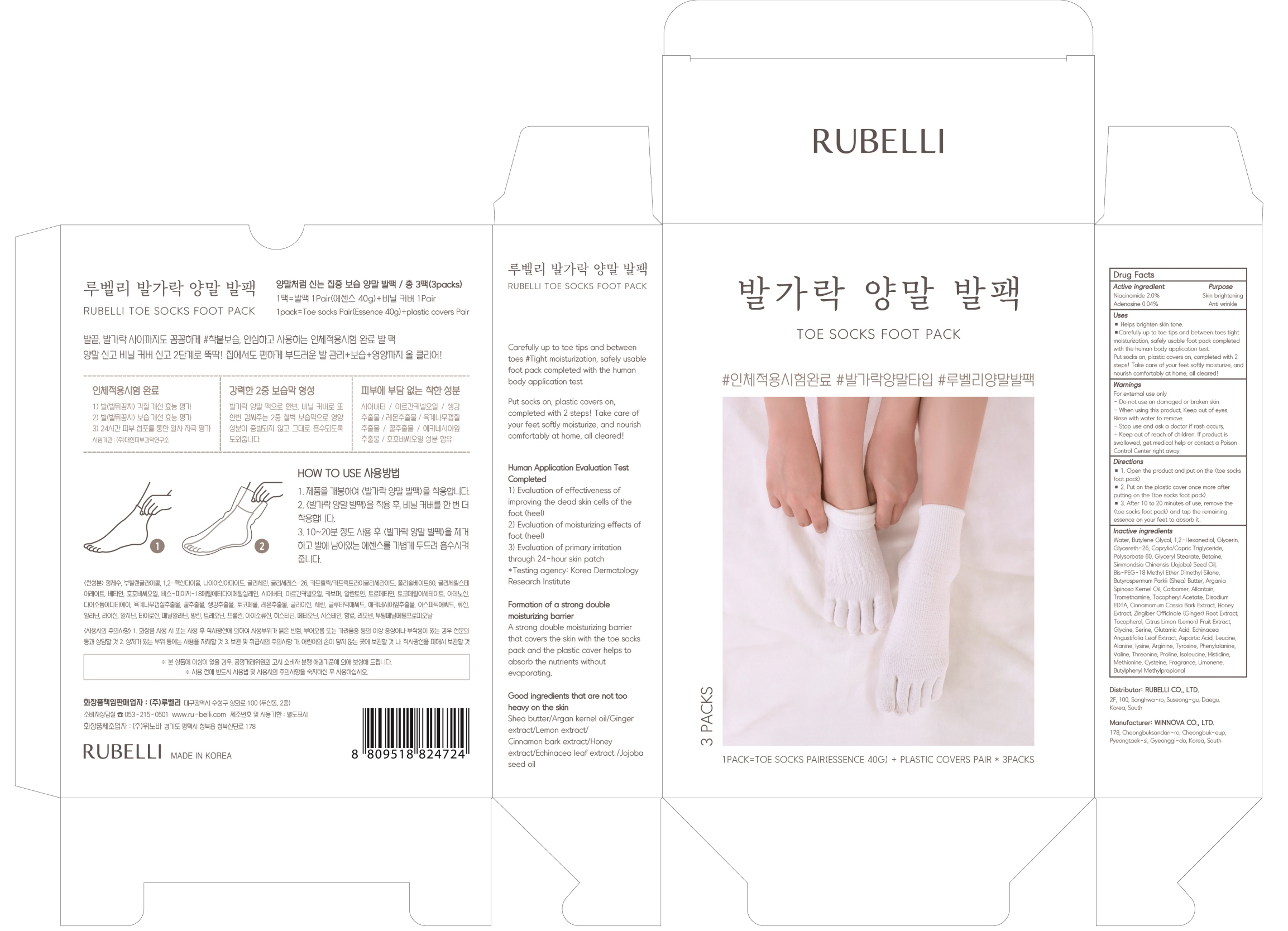 DRUG LABEL: RUBELLI TOE SOCKS FOOT PACK
NDC: 71006-100 | Form: LIQUID
Manufacturer: RUBELLI CO.,LTD
Category: otc | Type: HUMAN OTC DRUG LABEL
Date: 20210405

ACTIVE INGREDIENTS: Niacinamide 0.8 g/40 mL; Adenosine 0.016 g/40 mL
INACTIVE INGREDIENTS: Water; Butylene Glycol; 1,2-Hexanediol

ACTIVE INGREDIENTS

Niacinamide 2.0%
Adenosine 0.04%

INACTIVE INGREDIENTS

Water, Butylene Glycol, 1,2-Hexanediol, Glycerin, Glycereth-26, Caprylic/Capric Triglyceride, Polysorbate 60, Glyceryl Stearate, Betaine, Simmondsia Chinensis (Jojoba) Seed Oil, Bis-PEG-18 Methyl Ether Dimethyl Silane, Butyrospermum Parkii (Shea) Butter, Argania Spinosa Kernel Oil, Carbomer, Allantoin, Tromethamine, Tocopheryl Acetate, Disodium EDTA, Cinnamomum Cassia Bark Extract, Honey Extract, Zingiber Officinale (Ginger) Root Extract, Tocopherol, Citrus Limon (Lemon) Fruit Extract, Glycine, Serine, Glutamic Acid, Echinacea Angustifolia Leaf Extract, Aspartic Acid, Leucine, Alanine, lysine, Arginine, Tyrosine, Phenylalanine, Valine, Threonine, Proline, Isoleucine, Histidine, Methionine, Cysteine, Fragrance, Limonene, Butylphenyl Methylpropional

PURPOSE

Skin brightening
Anti wrinkle

WARNINGS

For external use only
- Do not use on damaged or broken skin
- When using this product, Keep out of eyes. Rinse with water to remove.
- Stop use and ask a doctor if rash occurs.
- Keep out of reach of children. If product is swallowed, get medical help or contact a Poison Control Center right away.

KEEP OUT OF REACH OF CHILDREN

If product is swallowed, get medical help or contact a Poison Control Center right away.

Uses

■ Helps brighten skin tone.
■Carefully up to toe tips and between toes tight moisturization, safely usable foot pack completed with the human body application test.
Put socks on, plastic covers on, completed with 2 steps! Take care of your feet softly moisturize, and nourish comfortably at home, all cleared!

Directions

■ 1. Open the product and put on the <toe socks foot pack>.
■ 2. Put on the plastic cover once more after putting on the <toe socks foot pack>,
■ 3. After 10 to 20 minutes of use, remove the <toe socks foot pack> and tap the remaining essence on your feet to absorb it.